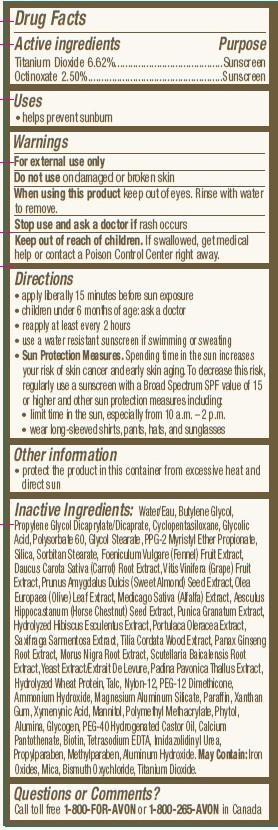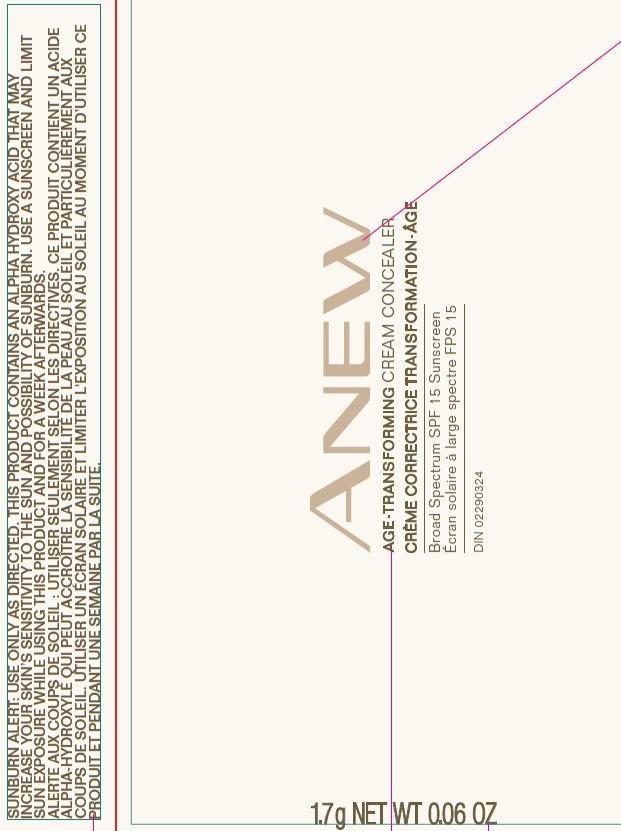 DRUG LABEL: Anew Age-Transforming
NDC: 10096-0138 | Form: CREAM
Manufacturer: New Avon LLC
Category: otc | Type: HUMAN OTC DRUG LABEL
Date: 20160301

ACTIVE INGREDIENTS: TITANIUM DIOXIDE 66.2 mg/1 g; OCTINOXATE 25 mg/1 g

Active ingredients
Titanium Dioxide 6.62%.........................
Octinoxate 2.50%.................................

Purpose
......................Sunscreen
.....................Sunscreen

Uses

- helps prevent sunburn

Warnings
For external use only

Do not use on damaged or broken skin

When using this product keep out of eyes. Rinse with water to remove.

Stop use and ask a doctor if rash occurs

Keep out of reach of children. If swallowed, get medical help or contact a Poison Control Center right away.

Directions

- apply liberally 15 minutes before sun exposure
- children under 6 months of age: ask a doctor
- reapply at least every 2 hours
- use a water resistant sunscreen if swimming or sweating
- Sun Protection Measures. Spending time in the sun increases your risk of skin cancer and early skin aging. To decrease this risk, regularly use a sunscreen with a Broad Spectrum SPF value of 15 or higher and other sun protection measures including:

- limit time in the sun, especially from 10 a.m. – 2 p.m.
- wear long-sleeved shirts, pants, hats, and sunglasses

Other information

- protect the product in this container from excessive heat and direct sun

INACTIVE INGREDIENT

Inactive Ingredients:Water/Eau, Butylene Glycol, Propylene Glycol Dicaprylate/Dicaprate, Cyclopentasiloxane, Glycolic Acid, Polysorbate 60, Glycol Stearate, PPG-2 Myristyl Ether Propionate, Silica, Sorbitan Stearate, Foeniculum Vulgare (Fennel) Fruit Extract, Daucus Carota Sativa (Carrot) Root Extract, Vitis Vinifera (Grape) Fruit Extract, Prunus Amygdalus Dulcis (Sweet Almond) Seed Extract, Olea Europaea (Olive) Leaf Extract, Medicago Sativa (Alfalfa) Extract, Aesculus Hippocastanum (Horse Chestnut) Seed Extract, Punica Granatum Extract,
Hydrolyzed Hibiscus Esculentus Extract, Portulaca Oleracea Extract, Saxifraga Sarmentosa Extract, Tilia Cordata Wood Extract, Panax Ginseng Root Extract, Morus Nigra Root Extract, Scutellaria Baicalensis Root Extract, Yeast Extract/Extrait De Levure, Padina Pavonica Thallus Extract, Hydrolyzed Wheat Protein, Talc, Nylon-12, PEG-12 Dimethicone, Ammonium Hydroxide, Magnesium Aluminum Silicate, Paraffin, Xanthan Gum, Xymenynic Acid, Mannitol, Polymethyl Methacrylate, Phytol, Alumina, Glycogen, PEG-40 Hydrogenated Castor Oil, Calcium Pantothenate, Biotin, Tetrasodium EDTA, Imidazolidinyl Urea, Propylparaben, Methylparaben, Aluminum Hydroxide. May Contain: Iron Oxides, Mica, Bismuth Oxychloride, Titanium Dioxide.

Questions or Comments?
Call toll free 1-800-FOR-AVON or 1-800-265-AVON in Canada